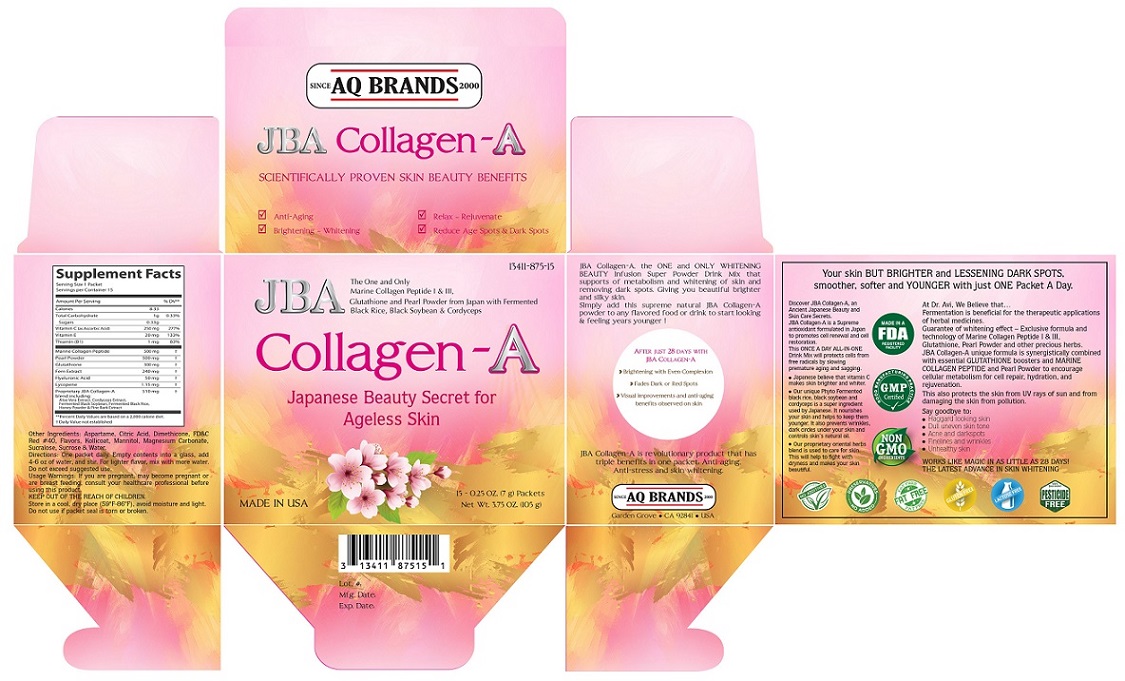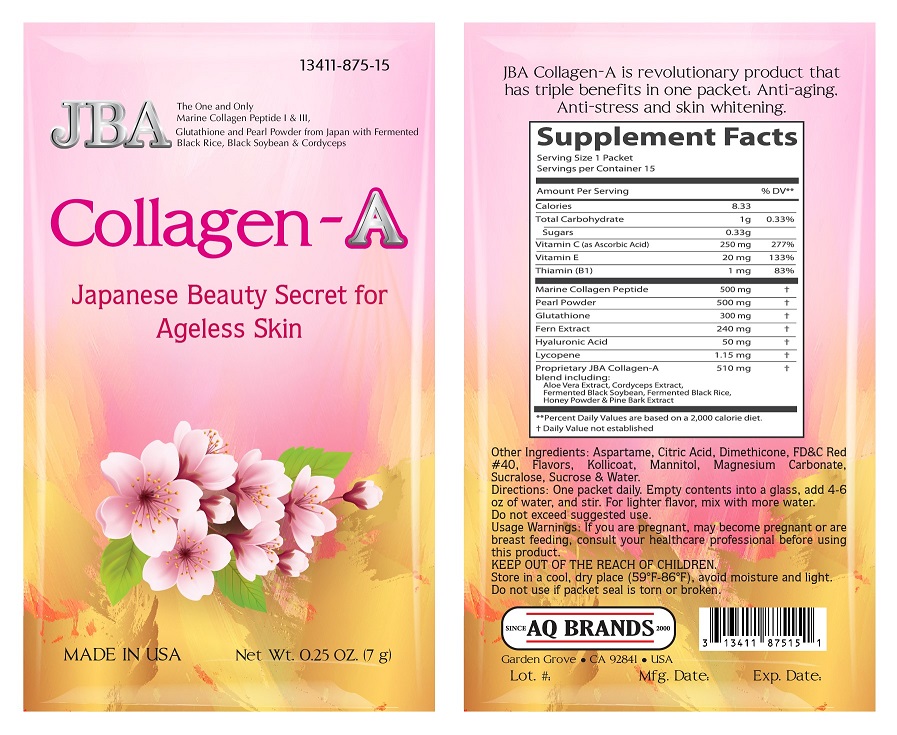 DRUG LABEL: JBA Collagen-A
NDC: 13411-875 | Form: POWDER
Manufacturer: Advanced Pharmaceutical Services, Inc. Dba Affordable Quality Pharmaceuticals
Category: other | Type: DIETARY SUPPLEMENT
Date: 20210616

ACTIVE INGREDIENTS: ASCORBIC ACID 250 mg/7 g; .ALPHA.-TOCOPHEROL 20 mg/7 g; THIAMINE 1 mg/7 g; MARINE COLLAGEN, SOLUBLE 500 mg/7 g; PEARL (HYRIOPSIS CUMINGII) 500 mg/7 g; GLUTATHIONE 300 mg/7 g; PHLEBODIUM AUREUM LEAF 120 mg/7 g; PHLEBODIUM AUREUM ROOT 120 mg/7 g; HYALURONIC ACID 50 mg/7 g; LYCOPENE 1.15 mg/7 g; ALOE VERA LEAF 50 mg/7 g; OPHIOCORDYCEPS SINENSIS 100 mg/7 g; SOYBEAN 100 mg/7 g; RICE BRAN 100 mg/7 g; MARITIME PINE 60 mg/7 g; HONEY 100 mg/7 g
INACTIVE INGREDIENTS: ASPARTAME; ANHYDROUS CITRIC ACID; DIMETHICONE; FD&C RED NO. 40; KOLLICOAT SR 30D; MANNITOL; SUCRALOSE; SUCROSE; MAGNESIUM CARBONATE; WATER

Identity

DIETARY SUPPLEMENT

Warning

If you are pregnant, may become pregnant or are breast feeding, consult your healthcare professional before using this product.

Dosage and administration

One packet daily. Empty contents into a glass, add 4-6 oz of water, and stir. For lighter flavor, mix with more water.
Do not exceed suggested use.

Safe handling warning

KEEP OUT OF THE REACH OF CHILDREN.
Store in a cool, dry place (59°F-86°F), avoid moisture and light.
Do not use if packet seal is torn or broken.

Health claim

SCIENTIFICALLY PROVEN SKIN BEAUTY BENEFITS
- Anti-Aging
- Brightening – Whitening
- Relax – Rejuvenate
- Reduce Age Spots & Dark Spots
-----------------------------------------
JBA Collagen-A, the ONE and ONLY WHITENING BEAUTY Infusion Super Powder Drink Mix that
supports of metabolism and whitening of skin and removing dark spots. Giving you beautiful
brighter and silky skin.
Simply add this supreme natural JBA Collagen-A powder to any flavored food or drink to start
looking & feeling years younger.
After just 28 days with JBA Collagen-A

Brightening with Even Complexion
- Fades Dark or Red Spots
- Visual improvements and anti-aging benefits observed on skin

JBA Collagen-A is a revolutionary product that has triple benefits in one packet: Anti-aging, Anti-stress and
skin whitening.

Your skin BUT BRIGHTER and LESSENING DARK SPOTS, smoother, softer and YOUNGER with just
ONE Packet A Day.
Discover JBA Collagen-A, an Ancient Japanese Beauty and Skin Care Secrets.
JBA Collagen-A is a Supreme antioxidant formulated in Japan to promotes cell renewal and cell restoration.
This ONCE A DAY ALL-IN-ONE Drink Mix will protect cells from free radicals by slowing premature
aging and sagging.
- Japanese believe that vitamin C makes skin brighter and whiter.
- Our unique Phyto Fermented black rice, black soybean and cordyceps is a super ingredient used
by Japanese. It nourishes your skin and helps to keep them younger. It also prevents wrinkles,
dark circles under your skin and controls skin’s natural oil.
- Our proprietary oriental herbs blend is used to care for skin. This will help to fight with dryness and
makes your skin beautiful.
At Dr. Avi, We Believe that…
Fermentation is beneficial for the therapeutic applications of herbal medicines.
Guarantee of whitening effect – Exclusive formula and technology of Marine Collagen Peptide I & III,
Glutathione, Pearl Powder and other precious herbs.
JBA Collage-A unique formula is synergistically combined with essential GLUTATHIONE booster and
MARINE COLLAGEN PEPTIDE and Pearl Powder to encourage cellular metabolism for cell repair,
hydration, and rejuvenation.
This also protects the skin from UV rays of sun and from damaging the skin from pollution.
Say goodbye to:
- Haggard looking skin
- Dull uneven skin tone
- Acne and dark spots
- Finelines and wrinkles
- Unhealthy skin
WORKS LIKE MAGIC IN AS LITTLE AS 28 DAYS!
THE LATEST ADVANCE IN SKIN WHITENING